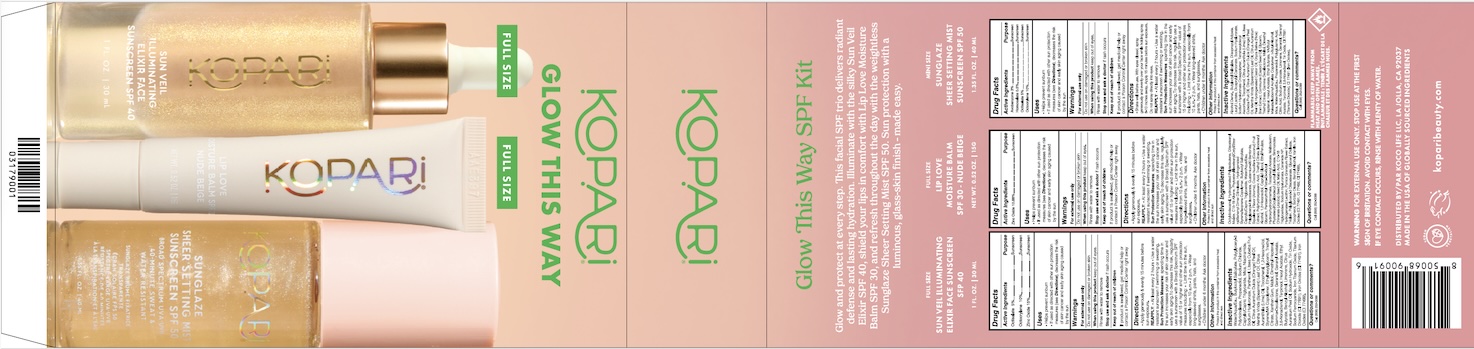 DRUG LABEL: Glow This Way
NDC: 84130-025 | Form: KIT | Route: TOPICAL
Manufacturer: Koco Life LLC
Category: otc | Type: HUMAN OTC DRUG LABEL
Date: 20260115

ACTIVE INGREDIENTS: HOMOSALATE 5 mg/1 mL; OCTISALATE 50 mg/1 mL; OCTOCRYLENE 100 mg/1 mL; AVOBENZONE 30 mg/1 mL; ZINC OXIDE 10.88 g/100 g; ZINC OXIDE 150 mg/1 mL; OCTOCRYLENE 100 mg/1 mL; OCTISALATE 50 mg/1 mL
INACTIVE INGREDIENTS: GLYCERIN; GERANIOL; TOCOPHEROL; RICE BRAN; GERANYL ACETATE; TITANIUM DIOXIDE; CITRIC ACID MONOHYDRATE; FERRIC OXIDE RED; SPEARMINT OIL; BITTER ORANGE OIL; BUTYLOCTYL SALICYLATE; HYALURONATE SODIUM; PEG-9 DIGLYCIDYL ETHER/SODIUM HYALURONATE CROSSPOLYMER; POLYGLUTAMIC ACID (1200 MW); ALCOHOL; 2,6-DIMETHYL-5-HEPTENAL; LIME OIL, COLD PRESSED; LIMONENE, (+)-; MALTOL; ETHYL BUTYRATE; TRIETHYL CITRATE; CASTOR OIL; MICA; SODIUM BENZOATE; ORANGE OIL, COLD PRESSED; LITSEA OIL; STANNOUS OXIDE; WATER; HYDROGENATED CASTOR OIL; TERPINEOL; .GAMMA.-DECALACTONE; PROPANEDIOL; TETRAHEXYLDECYL ASCORBATE; TERT-BUTYL ALCOHOL; HEXYL ACETATE; DIISOPROPYL ADIPATE; DICAPRYLYL CARBONATE; LAURYL LACTATE; DIBUTYL MALEATE; GLYCERIN; GLYCERYL DIOLEATE; SQUALANE; CI 77491; TRIETHYL CITRATE; HYDROGENATED POLYISOBUTENE 8; POLYHYDROXYSTEARIC ACID (2300 MW); CAPRYLYL GLYCOL; 1,2-HEXANEDIOL; JOJOBA OIL; PHYTOSTERYL/ISOSTEARYL/CETYL/STEARYL/BEHENYL DIMER DILINOLEATE; C15-19 ALKANE; HYDROGENATED SOYBEAN LECITHIN; CERAMIDE NP; CI 77499; WATER; DIISOSTEARYL MALATE; PENTAERYTHRITYL TETRA-DI-T-BUTYL HYDROXYHYDROCINNAMATE; TOCOPHEROL; SODIUM HYALURONATE; C10-18 TRIGLYCERIDES; ETHYL FERULATE; MALIC ACID; PUNICA GRANATUM FLOWER; SORBITAN OLEATE; ISOSTEARYL ALCOHOL; POLYGLYCERYL-4 ISOSTEARATE; POLYGLYCERYL-3 DIISOSTEARATE; PHYTOSTERYL/OCTYLDODECYL LAUROYL GLUTAMATE; VANILLIN; CAPRYLIC/CAPRIC TRIGLYCERIDE; MALTODEXTRIN; BENZYL ALCOHOL; CI 77492; QUATERNIUM-90 BENTONITE; COCOS NUCIFERA (COCONUT) FRUIT; .ALPHA.-TOCOPHEROL ACETATE; OCTYLDODECANOL; TRIOLEIN; BUTYLOCTYL SALICYLATE; BENZYL ALCOHOL; CITRUS AURANTIUM DULCIS (ORANGE) PEEL OIL; TITANIUM DIOXIDE; LIMONENE, (+)-; 3,6-NONADIEN-1-OL, (3Z,6Z)-; SODIUM HYDROXIDE; TIN OXIDE; NIACINAMIDE; MICA; ETHYL BUTYRATE; MALTOL; FERRIC TITANATE; PANTHENOL; POLYGLYCERYL-3 PENTARICINOLEATE; CI 77491; LITSEA CUBEBA FRUIT OIL; TOCOPHEROL; TRIETHYL CITRATE; XANTHAN GUM; CI 77499; GERANIOL; ETHYLHEXYLGLYCERIN; 1,2-HEXANEDIOL; WATER; PROPANEDIOL; CITRUS AURANTIFOLIA (LIME) OIL; SODIUM CHLORIDE; CAPRYLIC/CAPRIC TRIGLYCERIDE; TERPINEOL; DIMETHYL HEPTENAL; MENTHA VIRIDIS (SPEARMINT) LEAF OIL; BUTYLOCTYL SALICYLATE; CITRUS AURANTIUM PEEL OIL; GERANYL ACETATE; SODIUM FERROCYANIDE; SODIUM HYALURONATE; HEXYL ACETATE; GAMMA-DECALACTONE

Glow This Way Kit

84130-011 Sunglaze Sheer Setting Mist Sunscreen SPF50

Active ingredients

Avobenzone 3%, Homosalate 0.5%, Octisalate 5%, Octyocrylene 10%

Purpose

Avobenzone 3%, Homosalate 0.5%, Octisalate 5%, Octyocrylene 10%.................Sunscreen

Uses

• Helps prevent sunburn

• If used as directed with other sun protection measures(see Directions), decreases the risk of skin cancer & early skin aging caused by the sun.

Warnings

For external use only

● Do not use on damage or broken skin

● When using this product keep out of eyes. Rinse with water to remove.

● Stop use and ask a doctor if a rash occurs.

● Keep out of reach of children. If product is swallowed, get medical help or contact a Poison Control Center right away.

Directions

Shake well before use. With eyes closed, spray generously and evenlyover your face while holding spray 8-10 inches away. Apply 15 minutesbefore sun exposure. • Reapply: After 40 minutes of swimming orsweating. • Immediately after towel drying. • At least every 2 hours. Do notspray directly into eyes • Sun Protection Measures Spending time in thesun increases your risk of skin cancer & early skin aging. To decrease thisrisk, regularly use a sunscreen with a Broad Spectrum SPF value of 15 orhigher & other sun protection measures including: • Limit time in the sun,especially from 10 a.m. - 2 p.m. • Wear long-sleeved shirts, hats, andsunglasses • Children under 6 months of age: Ask a doctor

Inactive ingredients

Alcohol Denat., Butyloctyl Salicylate, Diisopropyl Adipate, Lauryl Lactate, Dicaprylyl Carbonate, Sodium Hyaluronate, Sodium Hyaluronate Crosspolymer, Tetrahexyldecyl Ascorbate, Tocopherol, Citrus Aurantifolia (Lime) Oil, Litsea Cubeba Fruit Oil, Citrus Aurantium Dulcis (Orange) Peel Oil, Mentha Viridis (Spearmint) Leaf Oil, Citrus Aurantium Peel Oil, Hydrogenated Castor Oil, Oryza Sativa (Rice) Bran Extract, Communis (Castor) Seed Oil, Glycerin, Triethyl Citrate, Gamma Decalactone, Maltol, Dimethyl Heptenal, Hexyl Acetate, Ethyl Butyrate, VA/Butyl Maleate/Isobornyl Acrylate Copolymer, t-Butyl Alcohol, Mica, Water/Aqua/Eau, Propanediol, Polyglutamic Acid, Citric Acid, Sodium Benzoate, Limonene, Geraniol, Geranyl Acetate, Terpineol, 3,6-Nonadienol, Tin Oxide, CI 77891 (Titanium DIoxide), CI 77491 (Iron Oxides).

Other information

• Protect this product fromexcessive heat and direct sun

• May stain some fabrics

Questions/Comments

Call (858) 252-0099

84130-015 Lip Love Moisture Balm SPF30 - Nude Beige

Active ingredient

Zinc Oxide 10.88%

Purpose

Zinc Oxide 10.88%...Sunscreen

Uses

• Helps prevent sunburn

• If used as directed with othersun protection measures(see Directions), decreases therisk of skin cancer and earlyskin aging caused by the sun

Warnings

For external use only

Do not use on damaged or broken skin

When using this product keep out of eyes

Rinse with water to remove

Stop use and ask a doctor if rash occurs

Keep out of reach of children
If product is swallowed , get medical help or contact a Poison Control Center right away

Directions

• Apply generously & evenly 15 minutes before sun exposure. REAPPLY: At least every 2 hours.

Sun Protection Measures: Spending time in the sun increases your risk of skin cancer and early skin aging. To decrease this risk, regularly use a sunscreen with a Broad Spectrum SPF value of 15 or higher and other sun protection measures including: • Limit time in the sun, especially from 10 a.m.- 2 p.m. • Wearlong-sleeved shirts, pants, hats, and sunglasses • Children under 6 months: Ask a doctor

Inactive ingredients

Octyldodecanol, Hydrogenated Polyisobutene, Diisostearyl Malate, C15-19 Alkane, Phytosteryl/Isostearyl/Cetyl/Stearyl/Behenyl Dimer Dilinoleate, Hydrogenated Styrene/Isoprene Copolymer, Butyloctyl Salicylate, Caprylic/Capric Triglyceride, Water/Aqua/Eau, Polyglyceryl-4 Isostearate, Quaternium-90 Bentonite, Squalane, Flavor (Aroma), Cocos Nucifera (Coconut) Fruit Extract, Polyhydroxystearic Acid, Triethyl Citrate, Isostearyl Alcohol, 1,2-Hexanediol, Caprylyl Glycol, Ethyl Ferulate, Glycerin, Pentaerythrityl Tetra-Di-t-Butyl Hydroxyhydrocinnamate, Tocopheryl Acetate, Maltodextrin, Phytosteryl/Octyldodecyl Lauroyl Glutamate, Simmondsia Chinensis (Jojoba) Seed Oil, Malic Acid, C10-18 Triglycerides, Sodium Hyaluronate, Ceramide NP, Hydrogenated Lecithin, Punica Granatum Flower Extract, Triolein, Polyglyceryl-3 Diisostearate, Glyceryl Dioleate, Tocopherol, Sorbitan Oleate, Benzyl Alcohol, Vanillin, Iron Oxides (CI 77491, CI 77492, CI 77499)

Other information

Protect the product in this container from excessive heat and direct sun

Questions or comments?

Call (858) 252-0099

84130-XXX Sun Veil Illuminating Elixir Face Sunscreen SPF 40

Active ingredients

Octisalate 5%

Octocrylene 10%

Zinc Oxide 15%

Purpose

Octisalate 5%.................Sunscreen

Octocrylene 10%.................Sunscreen

Zinc Oxide 15%.................Sunscreen

Uses

- Helps prevent sunburn
- If used as directed with other sun protection measures (see Directions), decreases the risk of skin cancer and early skin aging caused by the sun

Warnings

For external use only

Do not use on damaged or broken skin

When using this product keep out of eyes. Rinse with water to remove.

Keep out of reach of children. If product is swallowed, get medical help or contact a Poison Control Center right away.

Directions

- Apply generously & evenly 15 minutes before sun exposure

REAPPLY:

- At least every 2 hours
- Use a water resistant sunscreen if swimming or sweating

Sun Protection Measures: spending time in the sun increases your risk of skin cancer and early skin aging. To decrease this risk, regularly use sunscreen with a Broad Spectrum SPF value of 15 or higher and other sun protection measures including:

- Limit time in the sun, especially from 10 a.m.-2 p.m.
- Wear long-sleeved shirts, pants, hats, and sunglasses
- Children under 6 months: Ask doctor

Other information

Protect the product in this container from excessive heat and direct sun

Inactive ingredients

Water/Aqua/Eau, Butyloctyl Salicylate, Polyglyceryl-3 Polyricinoleate, Propanediol, Sodium Chloride, Caprylic/Capric Triglyceride, Mica, Niacinamide, Sodium Hyaluronate, Panthenol, Litsea Cubeba Fruit Oil, Citrus Aurantium Dulcis (Orange) Peel Oil, Mentha Viridis (Spearmint) Leaf Oil, Citrus Aurantifolia (Lime) Oil, Tocopherol, 1,2-Hexanediol, Styrene/MA Copolymer, Ethylhexylglycerin, Triethyl Citrate, Xanthan Gum, Maltol, Dimethyl Heptenal, Gamma-Decalactone, Geraniol, Geranyl Acetate, 3,6-Nonadienol, Terpineol, Hexyl Acetate, Ethyl Butyrate, Benzyl Alcohol, Limonene, Citrus Aurantium Peel Oil, Sodium Hydroxide, Tin Oxide, Sodium Ferrocyanide, Iron Titanium Oxide, Titanium Dioxide (CI 77891), Iron Oxides (CI 77491), Iron Oxides (CI 77499)

Questions or comments?

Call (858) 252-0099

PACKAGE LABEL

Kopari Glow This Way